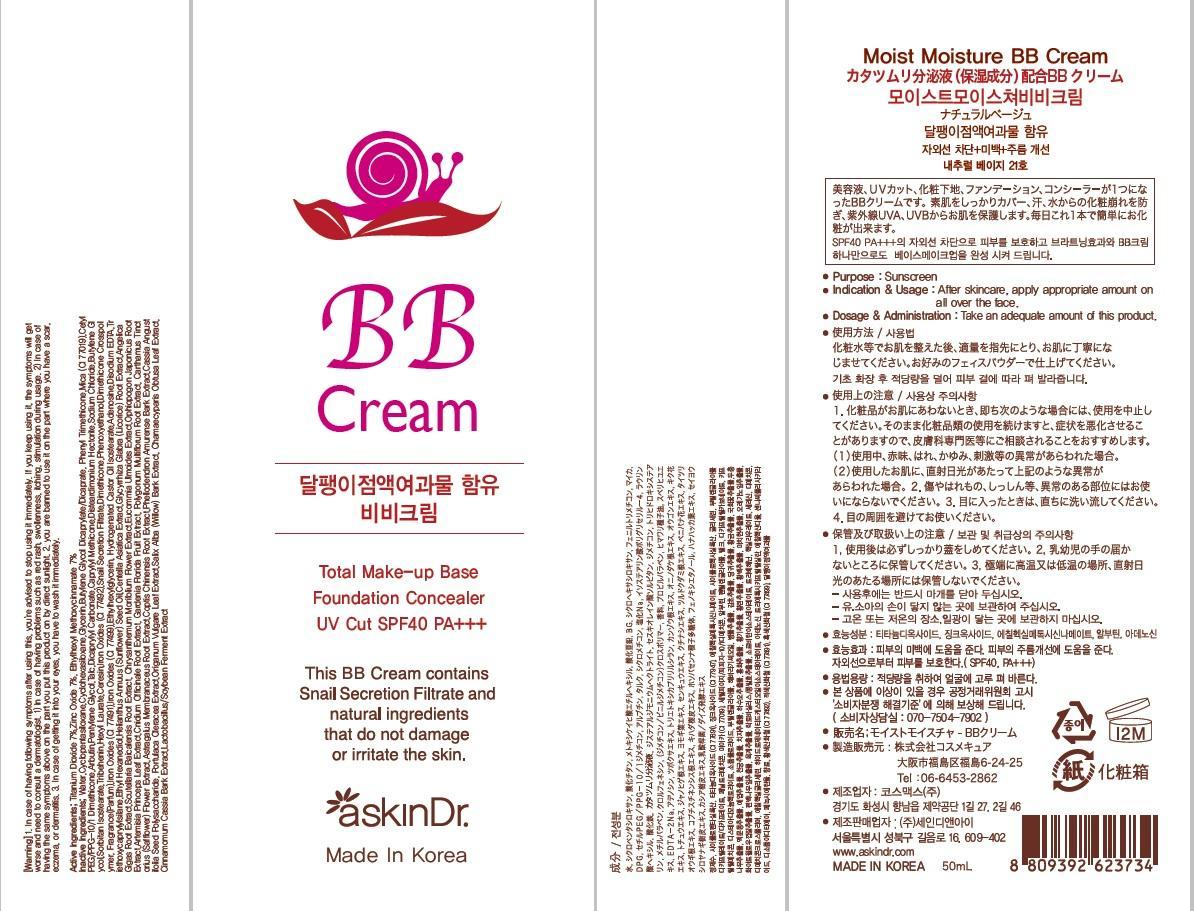 DRUG LABEL: MOIST MOISTURE BB
NDC: 69072-010 | Form: CREAM
Manufacturer: Seindni Co.,ltd
Category: otc | Type: HUMAN OTC DRUG LABEL
Date: 20181210

ACTIVE INGREDIENTS: Titanium Dioxide 3.5 mg/50 mL; Zinc Oxide 3.5 mg/50 mL; OCTINOXATE 3.5 mg/50 mL
INACTIVE INGREDIENTS: Water; Glycerin

ACTIVE INGREDIENT

Active Ingredients: Titanium Dioxide 7%, Zinc Oxide 7%, Ethylhexyl Methoxycinnamate 7%

INACTIVE INGREDIENT

Inactive Ingredients:
Water,Cyclopentasiloxane,Cyclohexasiloxane,Glycerin,Butylene Glycol Dicaprylate/Dicaprate, Phenyl Trimethicone,Mica (CI 77019),Cetyl PEG/PPG-10/1 Dimethicone,Arbutin,Pentylene Glycol,Talc,Dicaprylyl Carbonate,Caprylyl Methicone,Disteardimonium Hectorite,Sodium Chloride,Butylene Glycol,Sorbitan Isostearate,Tribehenin,Hexyl Laurate,Ceresin,Iron Oxides (CI 77492),Snail Secretion Filtrate,Dimethicone,Phenoxyethanol,Dimethicone Crosspolymer, Fragrance(Parfum),Iron Oxides (CI 77491),Iron Oxides (CI 77499),Ethylhexylglycerin, Hydrogenated Castor Oil Isostearate,Adenosine,Disodium EDTA,Triethoxycaprylylsilane,Ethyl Hexanediol,Helianthus Annuus (Sunflower) Seed Oil,Centella Asiatica Extract,Glycyrrhiza Glabra (Licorice) Root Extract,Angelica
Gigas Root Extract,Scutellaria Baicalensis Root Extract, Chrysanthemum Morifolium Flower Extract,Eucommia Ulmoides Extract,Ophiopogon Japonicus Root Extract,Artemisia Princeps Leaf Extract,Cnidium Officinale Root Extract, Gardenia Florida Fruit Extract, Polygonum Multiflorum Root Extract, Carthamus Tinctorius (Safflower) Flower Extract,Astragalus Membranaceus Root Extract,Coptis Chinensis Root Extract,Phellodendron Amurense Bark Extract,Cassia Angustifolia Seed Polysaccharide, Portulaca Oleracea Extract,Origanum Vulgare Leaf Extract,Salix Alba (Willow) Bark Extract, Chamaecyparis Obtusa Leaf Extract, Cinnamomum Cassia Bark Extract,Lactobacillus/Soybean Ferment Extract

PURPOSE

Purpose: Sunscreen

WARNINGS

Warning:
1. In case of having following symptoms after using this, you're advised to stop using it immediately. If you keep using it, the symptoms will get worse and need to consult a dermatologist.
1) In case of having problems such as red rash, swollenness, itching, stimulation during usage.
2) In case of having the same symptoms above on the part you put this product on by direct sunlight.
2. you are banned to use it on the part where you have a scar, eczema, or dermatitis.
3. In case of getting it into your eyes, you have to wash it immediately.

KEEP OUT OF REACH OF CHILDREN

INDICATIONS AND USAGE

Indication and Usage: After skincare, apply appropriate amount on all over the face.

Dosage and Administration : Take an adequate amount of this product.